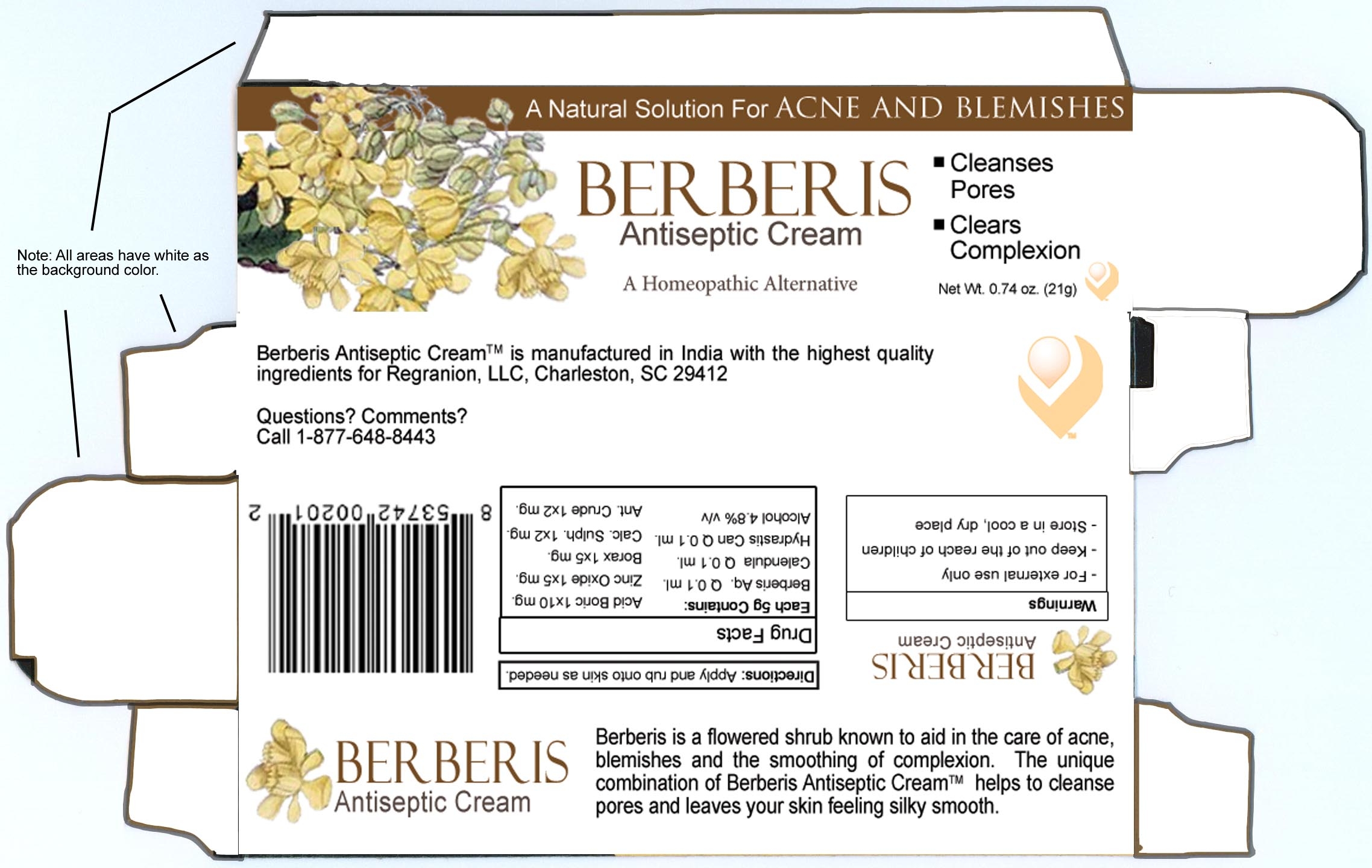 DRUG LABEL: Berberis
NDC: 51720-421 | Form: CREAM
Manufacturer: Curative Power Lab PVT LTD
Category: homeopathic | Type: HUMAN OTC DRUG LABEL
Date: 20101110

ACTIVE INGREDIENTS: MAHONIA AQUIFOLIUM ROOT BARK  2 [hp_X]/21 g; CALENDULA OFFICINALIS FLOWERING TOP 2 [hp_X]/21 g; GOLDENSEAL 2 [hp_X]/21 g; BORIC ACID 1 [hp_X]/21 g; ZINC OXIDE 1 [hp_X]/21 g; SODIUM BORATE 1 [hp_X]/21 g; CALCIUM SULFATE 1 [hp_X]/21 g; ANTIMONY TRISULFIDE 1 [hp_X]/21 g
INACTIVE INGREDIENTS: ALCOHOL 1 mL/21 g

Berberis

ACTIVE INGREDIENT

Berberis Aq. - 0.1ml
Calendula - 0.1ml
Hydrastis Can. - 0.1ml
Acid Boric - 1x 10mg
Zinc Oxide - 1x 5mg
Borax - 1x5mg
Calc. Sulph. - 1x 2mg
Ant. Crude - 1x 2mg

INACTIVE INGREDIENT

Alcohol - 4.8 percent v/v

PURPOSE

Berberis is a flowered shrub known to aid in the care of acne, blemishes, and the smoothing of complexion. The unique combination of Berberis Antiseptic Cream helps to cleanse pores and leaves your skin feeling silky smooth.

INDICATIONS AND USAGE

Berberis. A natural solution for acne and blemishes.

- Cleanses Pores

-Clears Complexion

DOSAGE AND ADMINISTRATION

Apply and rub onto skin as needed.

WARNINGS

- For external use only.

- Store in a cool, dry place.

Keep out of the reach of children.

HOW SUPPLIED

Berberis Antiseptic Cream is manufactured in India with the highest quality ingredients for Regranion, LLC, Charleston, SC 29403

REFERENCES

Questions? Comments?
Call 1-877-648-8443